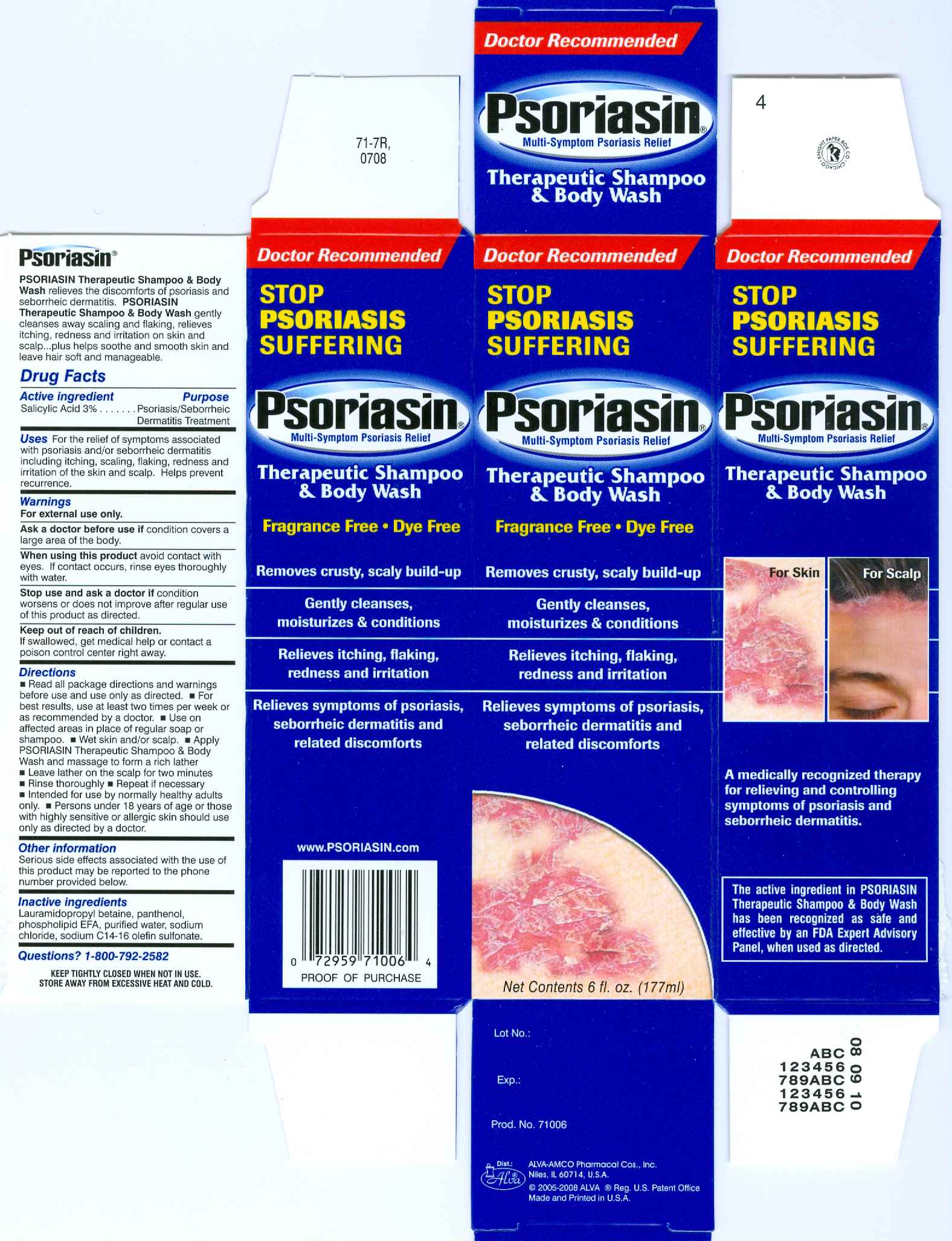 DRUG LABEL: Psoriasin
NDC: 52389-171 | Form: SHAMPOO
Manufacturer: Alva-Amco Pharmacal Companies, Inc.
Category: otc | Type: HUMAN OTC DRUG LABEL
Date: 20100507

ACTIVE INGREDIENTS: Salicylic acid 3 g/100 g
INACTIVE INGREDIENTS: Lauramidopropyl betaine; Panthenol; Lecithin, soybean; Water; Sodium chloride; Sodium C14-16 olefin sulfonate

Drug Facts

Active ingredient

Salicylic acid, 3%..................................Psoriasis/Seborrheic Dermatitis Treatment

Uses

For the relief of symptoms associated with psoriasis and/or seborrheic dermatitis including itching, flaking, redness and irritation of the skin and scalp. Helps prevent recurrence.

Warnings

For external use only.

Ask a doctor before use if condition covers a large area of the body.

When using this product avoid contact with eyes. If contact occurs, rinse eyes thoroughly with water.

Stop use and ask a doctor if condition worsens or does not improve after regular use of this product as directed.

Keep out of reach of children. If swallowed, get medical help or contact a poison control center right away.

Directions

- Read all package directions and warnings before use and use only as directed.
- For best results, use at least two times per week or as recommended by a doctor.
- Use on affected areas in place of regular soap or shampoo.
- Wet skin and/or scalp.
- Apply Psoriasin Therapeutic Shampoo and Body Wash and massage to form a rich lather.
- Leave lather on the scalp for two minutes.
- Rinse thoroughly.
- Repeat if necessary.
- Intended for use by normally healthy adults only.
- Persons under 18 years of age or those with highly sensitive or allergic skin should use only as directed by a doctor.

Other information

Serious side effects associated with the use of this product may be reported to the phone number provided below.

Inactive ingredients

Lauramidopropyl betaine, panthenol, phospholipid EFA, purified water, sodium chloride, sodium C14 - 16 olefin sulfonates.

Questions? 1-800-792-2582

Product Insert

PSORIASIN Therapeutic Shampoo and Body Wash

3% Salicylic Acid

- Relieves the symptoms of psoriasis, seborrheic dermatitis and related discomforts
- Cleans, soothes and moisturizes

A WORD ABOUT PSORIASIN THERAPEUTIC SHAMPOO and BODY WASH

PSORIASIN Therapeutic Shampoo and Body Wash relieves the discomforts of psoriasis and seborrheic dermatitis. PSORIASIN Therapeutic Shampoo and Body Wash cleanses away scaling and flaking, relieves itching, redness and irritation on skin and scalp ... plus helps soothe and smooth skin and leave hair soft and manageable.

WHAT IS PSORIASIS AND SEBORRHEIC DERMATITIS?

PSORIASIS is a non-contagious skin disorder that afflicts millions of men and women of all ages. Normal skin cells multiply, mature and shed on a regular basis. In those afflicted with psoriasis, skin cells appear to multiply much faster than normal, with excessive skin cells accumulating on the skin surface. In its most common form, these cells form scaly, reddish patches which are often unsightly, uncomfortable and are frequently irritating, itchy and painful. While the exact causes of psoriasis are still unknown, it is reported that a susceptibility to psoriasis may be inherited ... passed along from one generation to another genetically within families. First visible outbreaks of psoriasis may be prompted by a stress such as surgery, a major infection, or a minor skin injury such as a burn or cut. After the first outbreak, psoriasis flare-ups tend to come and go without any specific regularity or frequency, although symptoms appear to diminish during warm summer months and increase during cold winter months. Some studies have shown a relationship between psoriasis flare-ups and periods of emotional stress.

The number of flare-ups and their intensity may differ from case to case. Although there is no known cure for psoriasis, the active ingredient in PSORIASIN Therapeutic Shampoo and Body Wash has been proven to help effectively relieve and control the symptoms of psoriasis, as well as prevent recurrences.

SEBORRHEIC DERMATITIS is a distinctly different condition, though sometimes it is confused with psoriasis. Seborrheic dermatitis is an inflammation affecting areas of the skin rich in sebaceous (oil producing) glands commonly on the hairy areas of the body, such as the scalp. This troublesome skin disorder tends to be marked by skin cell proliferation and heightened sebaceous gland activity ... skin cells shed and become scaly, itchy, red and irritated. Affected areas tend to display oily looking, yellowish, scaly patches. People who tend toward oily skin are more likely to be affected. While seborrheic dermatitis and psoriasis are different disorders, highly visible symptoms of seborrheic dermatitis, such as intense itching and dandruff respond well (as well as psoriasis symptoms) to the active ingredient in PSORIASIN. These symptoms can be relieved and controlled, as well as recurrences prevented, with regular use of PSORIASIN Therapeutic Shampoo and Body Wash.

HOW DO YOU KNOW IF YOU HAVE PSORIASIS OR SEBORRHEIC DERMATITIS OF THE SCALP OR BODY?

In its most common form, known as plaque psoriasis, the condition is characterized by sharply defined raised reddish areas of skin or patches, typically covered with overlapping, rough, dry silvery scaling. Often times outbreaks are accompanied by itching and flaking at the affected site. In many cases skin is cracked, irritated and burning. Seborrheic dermatitis frequently affects the scalp and other areas rich in sebaceous (oil producing) glands. Seborrheic dermatitis tends to show up as thick, greasy, yellowish scales, accompanied by itching and irritation.

If you experience any type of unusual skin eruption(s) including those described here, contact your doctor to make the correct diagnosis and obtain professional advice. You may wish to show him/her PSORIASIN Therapeutic Shampoo and Body Wash and discuss its use for relief and prevention.

ACTIVE INGREDIENT: Salicylic Acid 3%

USES: For the relief of symptoms associated with psoriasis and/or seborrheic dermatitis including itching, scaling, flaking, redness and irritation of the skin and scalp. Helps prevent recurrence.

WARNINGS: For external use only. Ask a doctor before use if condition covers a large area of the body. When using this product avoid contact with eyes. If contact occurs, rinse eyes thoroughly with water. Stop use and ask a doctor if condition worsens or does not improve after regular use of this product as directed. Keep out of reach of children. If swallowed, get medical help or contact a poison control center right away.

DIRECTIONS: • Read all package directions and warnings before use and use only as directed . • For best results, use at least two times per week or as recommended by a doctor .• Use on affected areas in place of regular soap or shampoo . • Wet skin and/or scalp . • Apply PSORIASIN Therapeutic Shampoo and Body Wash and massage to form a rich lather. • Leave lather on the scalp for two minutes. • Rinse thoroughly. • Repeat if necessary . • Intended for use by normally healthy adults only . • Persons under 18 years of age or those with highly sensitive or allergic skin should use only as directed by a doctor.

OTHER INFORMATION: Serious side effects associated with the use of this product may be reported to the phone number provided below.

INACTIVE INGREDIENTS: Lauramidopropyl Betaine, Panthenol, Phospholipid EFA, Purified Water, Sodium Chloride, Sodium C14-16 Olefin Sulfonate.

QUESTIONS: 1-800-792-2582